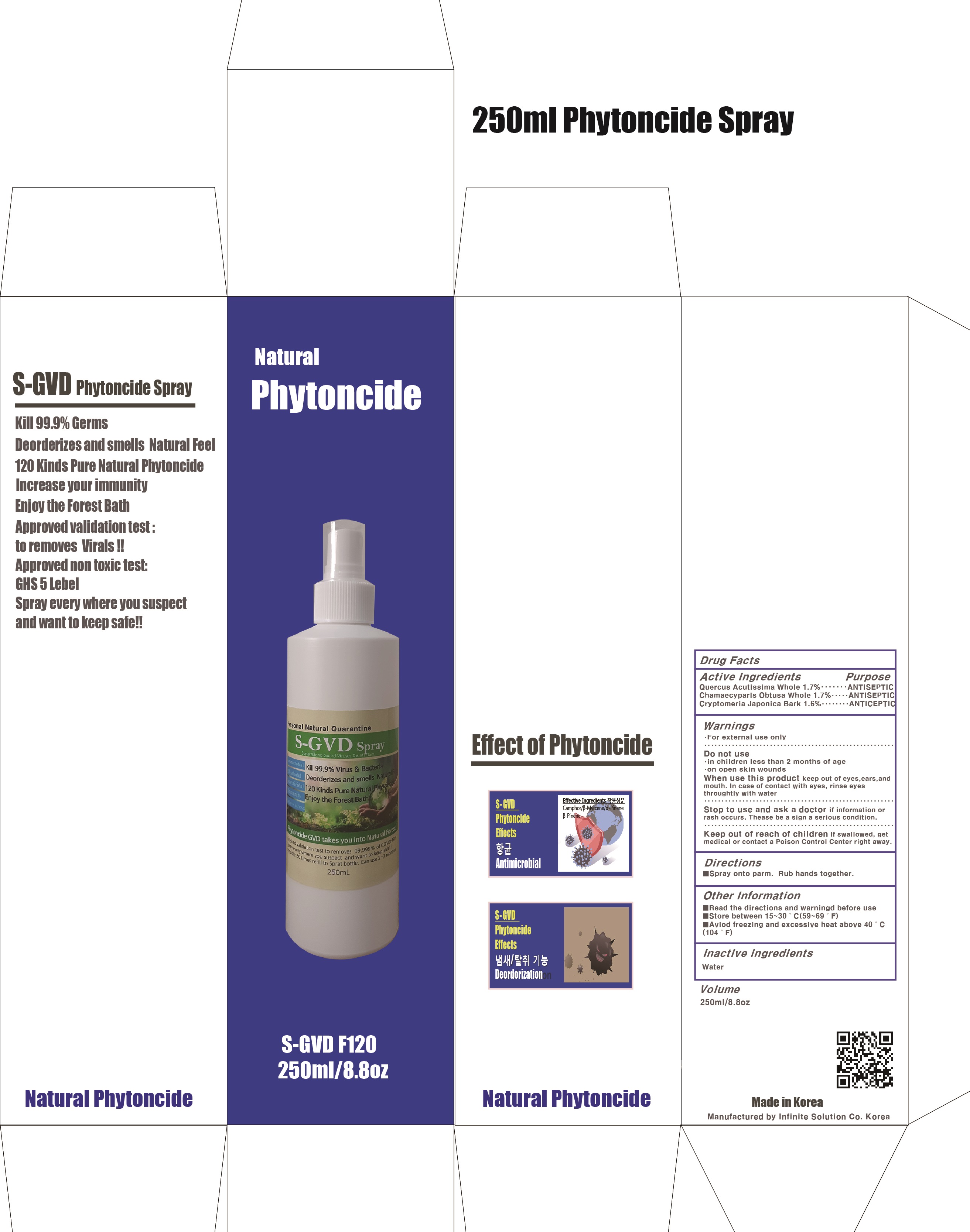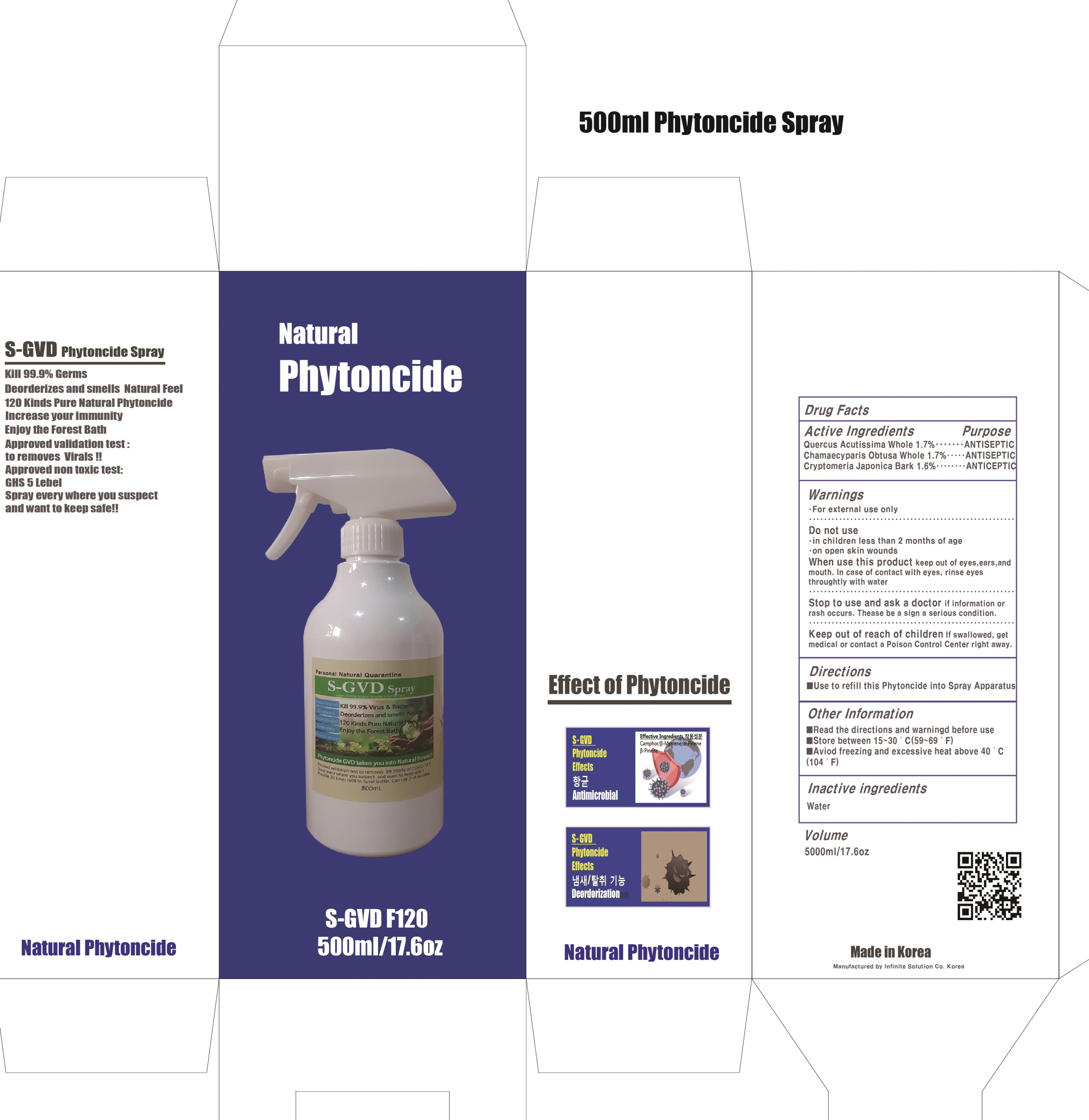 DRUG LABEL: S GVD Phytoncide
NDC: 81744-020 | Form: SPRAY
Manufacturer: Infinite Solution Co.
Category: otc | Type: HUMAN OTC DRUG LABEL
Date: 20210401

ACTIVE INGREDIENTS: QUERCUS ACUTISSIMA WHOLE 1.7 g/100 mL; CHAMAECYPARIS OBTUSA WHOLE 1.7 g/100 mL; CRYPTOMERIA JAPONICA BARK 1.6 g/100 mL
INACTIVE INGREDIENTS: Water

ACTIVE INGREDIENTS

Quercus Acutissima Whole 1.7%
Chamaecyparis Obtusa Whole 1.7%
Cryptomeria Japonica Bark 1.6%

INACTIVE INGREDIENT

Water

PURPOSE

ANTISEPTIC

WARNINGS

• For external use only
--------------------------------------------------------------------------------------------------------
Do not use
• in children less than 2 months of age
• on open skin wounds
--------------------------------------------------------------------------------------------------------
When using this product keep out of eyes, ears, and mouth. In case of contact with eyes, rinse eyes thoroughly with water.
--------------------------------------------------------------------------------------------------------
Stop use and ask a doctor if irritation or rash occurs. These may be signs of a serious condition.

KEEP OUT OF REACH OF CHILDREN

If swallowed, get medical help or contact a Poison Control Center right away.

Uses

Hand sanitizing to help reduce bacteria that potentially can cause disease.

Directions

Spray onto palm. Rub hands together.

Other Information

■ Read the directions and warnings before use
■ Store between 15-30℃(59-89℉)
■ Avoid freezing and excessive heat above 40℃(104 ℉)